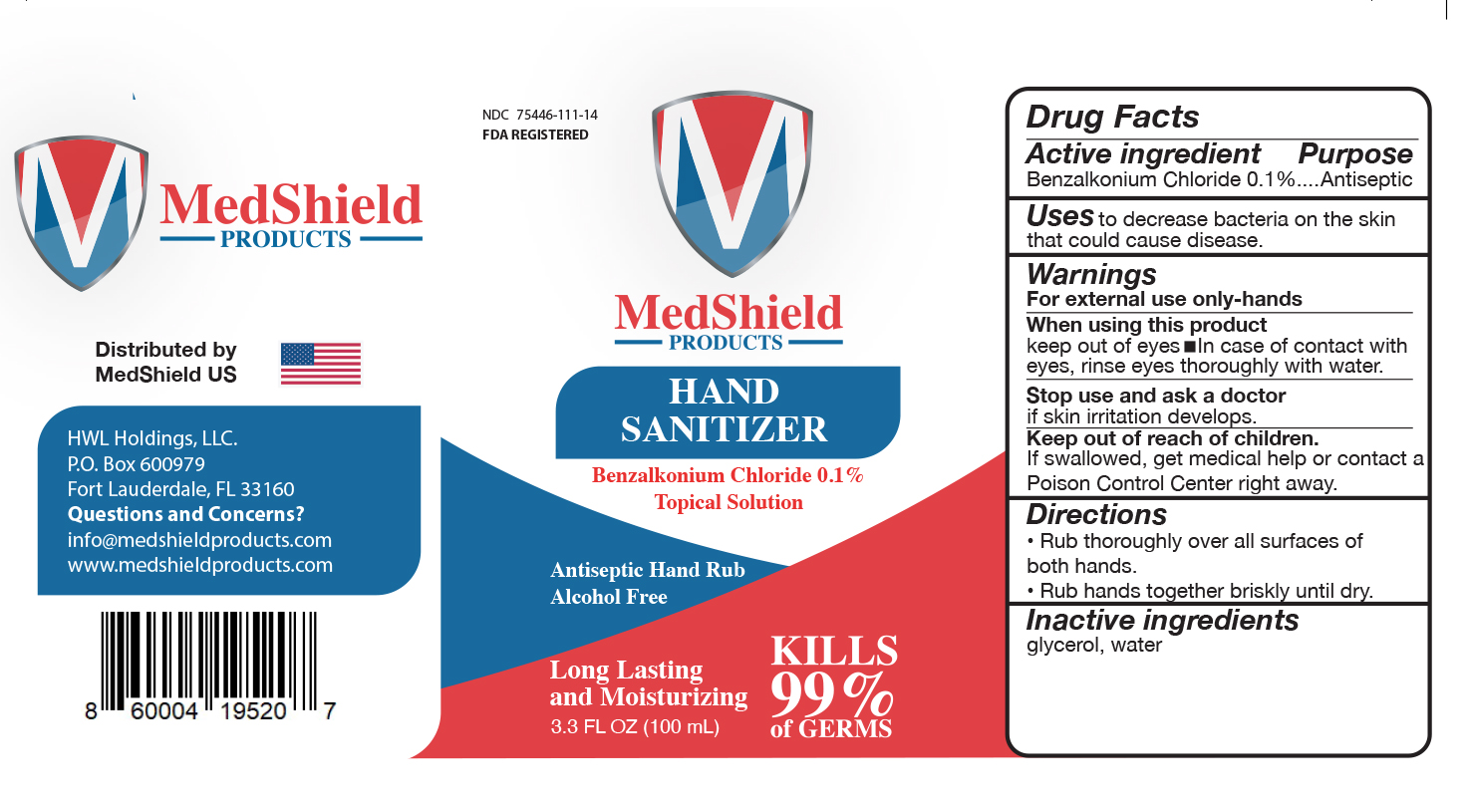 DRUG LABEL: MedShield Products
NDC: 75446-111 | Form: LIQUID
Manufacturer: HWL Holdings, LLC
Category: otc | Type: HUMAN OTC DRUG LABEL
Date: 20211209

ACTIVE INGREDIENTS: BENZALKONIUM CHLORIDE 1 ug/1 mL
INACTIVE INGREDIENTS: GLYCERIN; WATER

MedShield Liquid

Active Ingredient(s)

Benzalkonium Chloride 0.1% Purpose: Antiseptic

Purpose

Antiseptic, Hand Sanitizer

Use

to decrease bacteria on the skin that could cause disease

Warnings

For external use only-hands

WHEN USING

keep out of eyes In case of contact with eyes, rinse eyes thoroughly with water.

STOP USE

if skin irritation develops.

Keep out of reach of children. If swallowed, get medical help or contact a Poison Control Center right away.

Directions

- Rub thoroughly over all the surfaces of both hands.
- Rub hands together briskly until dry.

Inactive ingredients

glycerol, purified water USP

Package Label - Principal Display Panel

100 mL NDC: 75446-111-14